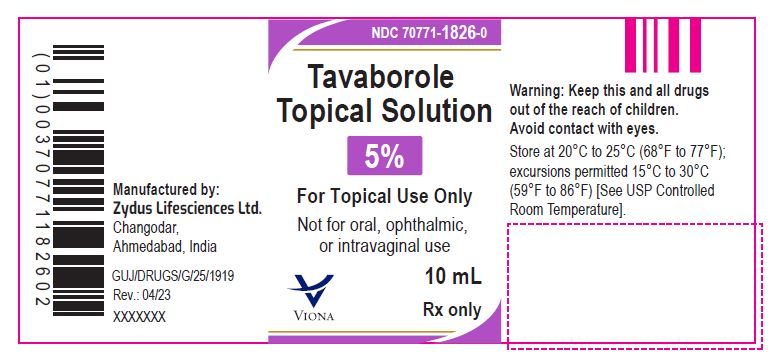 DRUG LABEL: Tavaborole
NDC: 70771-1826 | Form: SOLUTION
Manufacturer: Zydus Lifesciences Limited
Category: prescription | Type: HUMAN PRESCRIPTION DRUG LABEL
Date: 20241206

ACTIVE INGREDIENTS: TAVABOROLE 43.5 mg/1 mL
INACTIVE INGREDIENTS: ALCOHOL; EDETATE CALCIUM DISODIUM; PROPYLENE GLYCOL

Tavaborole Topical Solution

PACKAGE LABEL.PRINCIPAL DISPLAY PANEL

NDC 70771-1826-0

Tavaborole topical solution, 5%

10 mL

Rx only